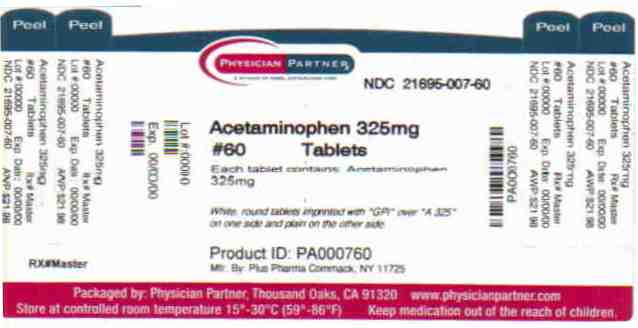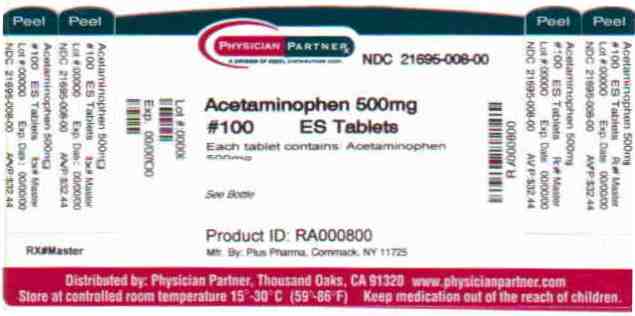 DRUG LABEL: Acetaminophen
NDC: 21695-007 | Form: TABLET
Manufacturer: Rebel Distributors Corp
Category: otc | Type: HUMAN OTC DRUG LABEL
Date: 20110214

ACTIVE INGREDIENTS: ACETAMINOPHEN 325 mg/1 1
INACTIVE INGREDIENTS: CROSPOVIDONE; POVIDONE; STARCH, CORN; STEARIC ACID

Acetaminophen Drug Facts

Active ingredient

Acetaminophen 325mg

Acetaminophen 500mg

Keep Out of Reach of Children

Taking more than the recommended dose (overdose) may cause liver damage. In case of overdose get medical help or contact a Poison Control Center immediately. Quick medical attention is critical for adults as well as children, even if you do not notice symptoms or signs.

Uses

Use for temporary relief of minor aches and pains due to:

° headache ° muscular aches ° backache ° arthritis ° the common cold ° toothache ° menstrual cramps ° temporarily reduces fever

Warnings

Alcohol Warning: If you consume 3 or more alcoholic beverages every day, ask your doctor whether you should take Acetaminophen or other pain relievers/fever reducers. Acetaminophen may cause liver damage.

Do not use with any other product containing Acetaminophen or if you have ever had an allergic reaction to pain relievers/fever reducers.

Stop use and ask a doctor if

° new symptoms occur ° redness or swelling is present ° pain gets worse or lasts more than 10 days ° fever gets worse or lasts more than 3 days.

If pregnant or breast-feeding, ask a doctor before use.

Directions

Do not take more than directed

° adults and children 12 years and older, take 2 tablets every 4 to 6 hours as needed. Do not take more than 12 tablets in 24 hours. ° children under 12, consult a doctor before use.

Other Information

For your protection, this bottle has an imprinted Safety Seal under cap. Do not use if Safety Seal is broken or missing.

Store at room temperature.

Questions? To report an adverse drug effect, contact 1-800-795-9775.

Inactive ingredients

Crospovidone, Povidone, Pregelatinized Starch, Stearic Acid.

Distributed by:

Plus PharmaCommack

New York 11725

Repackaged by:

Rebel Distributors Corp

Thousand Oaks, CA 91320